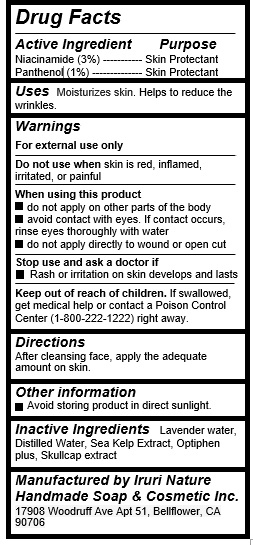 DRUG LABEL: Green Toner
NDC: 71547-101 | Form: LIQUID
Manufacturer: Iruri Nature Handmade Soap & Cosmetic Inc
Category: otc | Type: HUMAN OTC DRUG LABEL
Date: 20190103

ACTIVE INGREDIENTS: NIACINAMIDE 0.9 g/30 mL; PANTHENOL 0.3 g/30 mL
INACTIVE INGREDIENTS: WATER; SCUTELLARIA LATERIFLORA

Green Toner (Lavender Water & Sea Kelp Extract)

Active Ingredients

Niacinamide (3%)

Panthenol (1%)

Purpose

Skin protectant

Uses

Moisturizes skin. Helps to reduce the wrinkles.

Keep out of reach of children

If swallowed, get medical help or contact a Poison Control Center (1-800-222-1222) right away.

Warnings

For external use only

Do not use when skin is red, inflamed, irritated, or painful

When using this product

- do not apply on other parts of the body

- avoid contact with eyes. If contact occurs, rinse eyes thoroughly with water

- do not apply directly to wound or open cut

Stop use and ask a doctor if

- Rash or irritation on skin develops and lasts

Directions

After cleansing face, apply the adequate amount on skin.

Inactive Ingredients

Lavender water, Distilled Water, Sea Kelp Extract, Optiphen plus, Skullcap extract